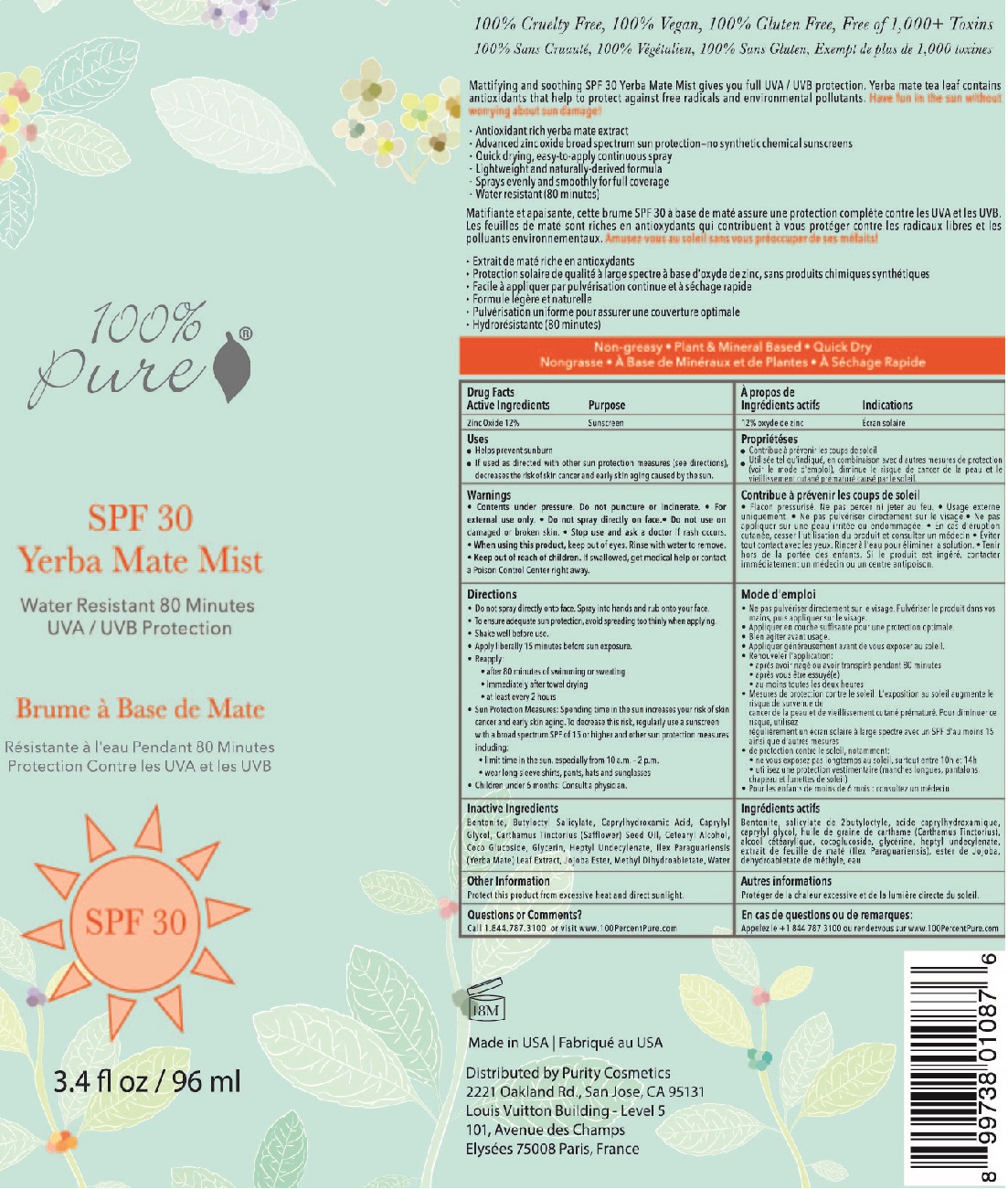 DRUG LABEL: 100% Pure Yerba Mate MIst
NDC: 52667-006 | Form: AEROSOL, SPRAY
Manufacturer: Purity Cosmetics
Category: otc | Type: HUMAN OTC DRUG LABEL
Date: 20170501

ACTIVE INGREDIENTS: ZINC OXIDE 120 mg/1 mL
INACTIVE INGREDIENTS: COCO GLUCOSIDE; HEPTYL UNDECYLENATE; ILEX PARAGUARIENSIS LEAF; WATER; GLYCERIN; BUTYLOCTYL SALICYLATE; SAFFLOWER OIL; CETOSTEARYL ALCOHOL; METHYL DIHYDROABIETATE; BENTONITE; CAPRYLHYDROXAMIC ACID; CAPRYLYL GLYCOL; JOJOBA OIL, RANDOMIZED

100% Pure Yerba Mate Mist SPF 30

Active Ingredients

Zinc Oxide 12%

Purpose

Sunscreen

Uses

- Helps prevent sunburn.
- If used as directed with other sun protection measures (see Directions), decreases the risk of skin cancer and early aging caused by the sun.

Warnings

- Contents under pressure. Do not puncture or incinerate.
- For external use only
- Do not spray directly on face.
- Do not use on damaged or broken skin.
- S top use and ask a doctor if rash occurs.
- When using this product keep out of eyes. Rinse with water to remove.

When using this product, keep out of eye. Rinse with water to remove.

Keep out of reach of children. If swallowed, get medical help or contact a Poison Control Center right away.

Directions

- Do not spray directly onto face. Spray into hands and rub onto your face.
- To ensure adequate sun protection, avoid spreading too thinly when applying.
- Shake well before use.
- Apply liberally 15 minutes before sun exposure.
- Reapply: after 80 minutes of swimming or sweating / immediately after towel drying / at least every 2 hours
- Sun Protection Measures: Spending time in the sun increases your risk of skin cancer and early skin aging. To decrease this risk, regularly use a sunscreen with a broad spectrum SPF of 15 or higher and other sun protection measures including:
- Limit time in the sun, especially from 10 a.m. - 2 p.m.
- Wear long-sleeved shirts, pants, hats and sunglasses.
- Children under 6 months: Consult a physician.

Other Ingredients

Bentonite, Butyloctyl Salicylate, Caprylhydroxamic Acid, Caprylyl Glycol, Carthamus Tinctorius (Safflower) Seed Oil, Cetearyl Alcohol, Coco Glucoside, Glycerin, Heptyl Undecylenate, Ilex Paraguariensis (Yerba Mate) Leaf Extract, Jojoba Ester, Methyl Dihydroabietate, Water

Other information

Protect this product from excessive heat and direct sunlight.

Questions or comments?

call 1.844.787.3100 or visit www.100PercentPure.com